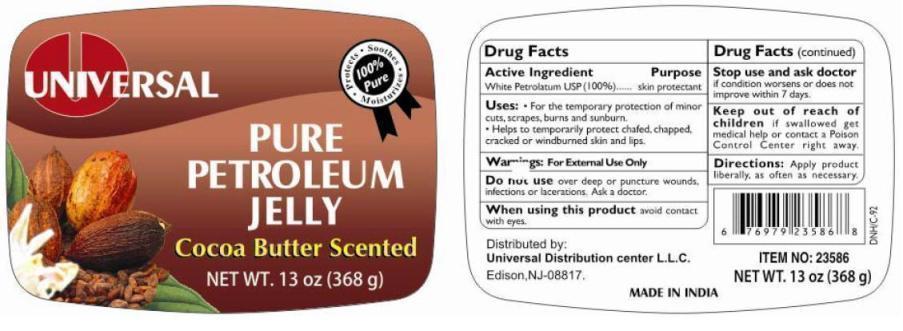 DRUG LABEL: UNIVERSAL PURE PETROLEUM COCOA BUTTER SCENTED
NDC: 52000-007 | Form: JELLY
Manufacturer: Universal Distribution Center LLC
Category: otc | Type: HUMAN OTC DRUG LABEL
Date: 20241015

ACTIVE INGREDIENTS: PETROLATUM 1 g/1 g
INACTIVE INGREDIENTS: .ALPHA.-TOCOPHEROL ACETATE 0.0001 g/1 g

Active ingredient

White Petrolatum USP (100 %)

Purpose

Skin Protectant

Uses

- For the temporary protection of minor cuts, scrapes, burns and sunburn.
- Helps to temporarily protect chafed, chapped, cracked or windburned skin and lips.

Warnings

For External Use Only.

Do not use over deep or puncture wounds, infections or lacerations. Ask a doctor.

When using this product avoid contact with eyes.

Stop use and ask doctor if condition worsens or does not improve within 7 days.

Keep out of reach of children if swallowed get medical help or contact a Poison Control Center right away.

Directions

Apply product as liberally, as often as necessary.

Inactive ingredients

None

PRINCIPAL DISPLAY PANEL

UNIVERSAL PURE PETROLEUM COCOA BUTTER SCENTED JELLY
SKIN PROTECTANT
NET WT. 13 OZ (368 g)